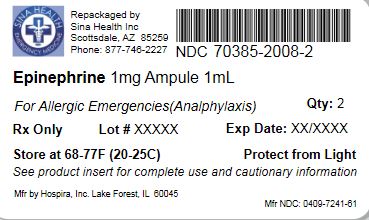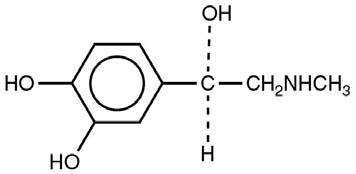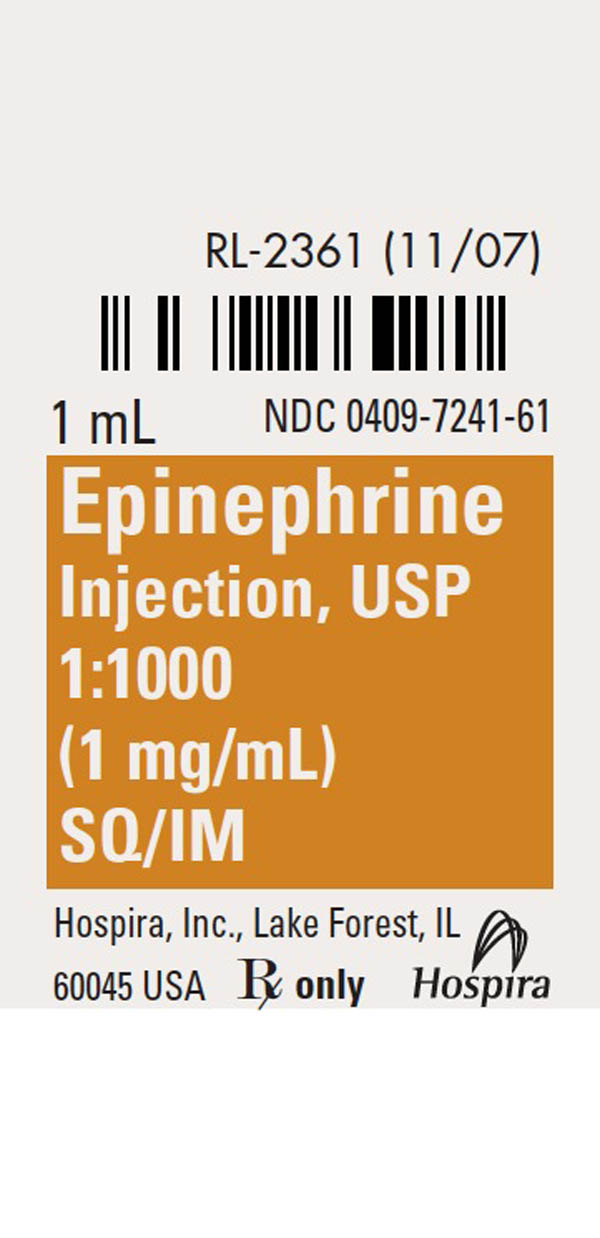 DRUG LABEL: Epinephrine
NDC: 70385-2008 | Form: INJECTION, SOLUTION
Manufacturer: Sina Health Inc
Category: prescription | Type: HUMAN PRESCRIPTION DRUG LABEL
Date: 20190204

ACTIVE INGREDIENTS: EPINEPHRINE 1 mg/1 mL
INACTIVE INGREDIENTS: SODIUM CHLORIDE; SODIUM METABISULFITE; HYDROCHLORIC ACID

EPINEPHRINE
Injection, USP

1:1000 (1 mg/mL)

Ampul

Protect from light until ready to use.

Rx only

DESCRIPTION

Epinephrine Injection, USP 1:1000 is a sterile, nonpyrogenic solution. Each mL contains epinephrine 1 mg; sodium chloride 9 mg; sodium metabisulfite 0.9 mg added. May contain hydrochloric acid for pH adjustment.

The solution contains no bacteriostat or antimicrobial agent. It is administered by the following routes: intravenous, intracardiac (left ventricular chamber), via endotracheal tube into the bronchial tree, subcutaneous or intramuscular.

Epinephrine, USP is a sympathomimetic (adrenergic) agent designated chemically as 4‑[1‑hydroxy-2 (methylamino) ethyl]-1,2 benzenediol, a white, microcrystalline powder. It has the following structural formula:

Sodium Chloride, USP is chemically designated NaCl, a white, crystalline compound freely soluble in water.

CLINICAL PHARMACOLOGY

The actions of epinephrine resemble the effects of stimulation of adrenergic nerves. To a variable degree it acts on both alpha and beta receptor sites of sympathetic effector cells. Its most prominent actions are on the beta receptors of the heart, vascular and other smooth muscle. When given by rapid intravenous injection, it produces a rapid rise in blood pressure, mainly systolic, by (1) direct stimulation of cardiac muscle which increases the strength of ventricular contraction, (2) increasing the heart rate and (3) constriction of the arterioles in the skin, mucosa and splanchnic areas of the circulation.

When given by slow intravenous injection epinephrine usually produces only a moderate rise in systolic and a fall in diastolic pressure. Although some increase in pulse pressure occurs, there is usually no great elevation in mean blood pressure. Accordingly, the compensatory reflex mechanisms that come into play with a pronounced increase in blood pressure do not antagonize the direct cardiac actions of epinephrine as much as with catecholamines that have a predominant action on alpha receptors.

Total peripheral resistance decreases by action of epinephrine on beta receptors of the skeletal muscle vasculature and blood flow is thereby enhanced. Usually this vasodilator effect of the drug on the circulation predominates so that the modest rise in systolic pressure which follows slow injection or absorption is mainly the result of direct cardiac stimulation and increase in cardiac output. In some instances peripheral resistance is not altered or may even rise owing to a greater ratio of alpha to beta activity in different vascular areas.

Epinephrine relaxes the smooth muscles of the bronchi and iris and is a physiologic antagonist of histamine. The drug also produces an increase in blood sugar and glycogenolysis in the liver.

Intravenous injection produces an immediate and intensified response. Following intravenous injection epinephrine disappears rapidly from the blood stream.

Epinephrine is rapidly inactivated in the body and is degraded by enzymes in the liver and other tissues. The large portion of injection doses is excreted in the urine as inactivated compounds. The remainder is excreted in the urine as unchanged or conjugated compounds.

INDICATIONS AND USAGE

Epinephrine is used to relieve respiratory distress due to bronchospasm, to provide rapid relief of hypersensitivity reactions to drugs and other allergens, and to prolong the action of anesthetics. Its cardiac effects may be of use in restoring cardiac rhythm in cardiac arrest due to various causes, but it is not used in cardiac failure or in hemorrhagic, traumatic, or cardiogenic shock. Epinephrine is used as a hemostatic agent. It is also used in treating mucosal congestion of hay fever, rhinitis, and acute sinusitis; to relieve bronchial asthmatic paroxysms; in syncope due to complete heart block or carotid sinus hypersensitivity; for symptomatic relief of serum sickness, urticaria, angioneurotic edema; for resuscitation in cardiac arrest following anesthetic accidents; in simple (open angle) glaucoma; for relaxation of uterine musculature and to inhibit uterine contractions. Epinephrine Injection can be utilized to prolong the action of anesthetics used in local and regional anesthesia.

CONTRAINDICATIONS

Epinephrine is contraindicated in patients with known hypersensitivity to sympathomimetic amines, in patients with angle closure glaucoma, and patients in shock (nonanaphylactic). It should not be used in patients anesthetized with agents such as cyclopropane or halothane as these may sensitize the heart to the arrhythmic action of sympathomimetic drugs. Addition of epinephrine to local anesthetics for injection of certain areas (e.g., fingers, toes, ears, etc.) is contraindicated because of danger that vasoconstriction may result in sloughing of tissue.

Except as diluted for admixture with local anesthetics to reduce absorption and prolong action, epinephrine should not ordinarily be used in those cases where vasopressor drugs may be contraindicated, e.g., in thyrotoxicosis, diabetes, in obstetrics when maternal blood pressure is in excess of 130/80 and in hypertension and other cardiovascular disorders.

WARNINGS

Inadvertently induced high arterial blood pressure may result in angina pectoris, aortic rupture or cerebral hemorrhage.

Epinephrine may induce potentially serious cardiac arrhythmias in patients not suffering from heart disease and in patients with organic heart disease or who are receiving drugs that sensitize the myocardium.

Parenterally administered epinephrine initially may produce constriction of renal blood vessels and decrease urine formation.

Epinephrine Injection, USP is subject to oxidation and should be protected against exposure to light and stored in light-resistant containers.

Epinephrine is the preferred treatment for serious allergic or other emergency situations even though this product contains sodium metabisulfite, a sulfite that may in other products cause allergic-type reactions including anaphylactic symptoms or life-threatening or less severe asthmatic episodes in certain susceptible persons. The alternatives to using epinephrine in a life-threatening situation may not be satisfactory. The presence of a sulfite in this product should not deter administration of the drug for treatment of serious allergic or other emergency situations.

PRECAUTIONS

Do not use the Injection if its color is pinkish or darker than slightly yellow or if it contains a precipitate.

Do not administer unless solution is clear and container is intact. Discard unused portion.

Although epinephrine can produce ventricular fibrillation, its actions in restoring electrical activity in asystole and in enhancing defibrillation of the fibrillating ventricle are well documented. The drug, however, should be used with caution in patients with ventricular fibrillation.

Epinephrine should be used cautiously in patients with hyperthyroidism, hypertension and cardiac arrhythmias. All vasopressors should be used cautiously in patients taking monoamine oxidase (MAO) inhibitors.

Epinephrine should not be administered concomitantly with other sympathomimetic drugs (such as isoproterenol) because of possible additive effects and increased toxicity. Combined effects may induce serious cardiac arrhythmias. They may be administered alternately when the preceding effect of other such drugs has subsided.

Administration of epinephrine to patients receiving cyclopropane or halogenated hydrocarbon general anesthetics such as halothane which sensitize the myocardium, may induce cardiac arrhythmia. (See CONTRAINDICATIONS.) When encountered, such arrhythmias may respond to administration of a beta-adrenergic blocking drug. Epinephrine also should be used cautiously with other drugs (e.g., digitalis glycosides) that sensitize the myocardium to the actions of sympathomimetic agents.

Diuretic agents may decrease vascular response to pressor drugs such as epinephrine. Epinephrine may antagonize the neuron blockade produced by guanethidine resulting in decreased antihypertensive effect and requiring increased dosage of the latter.

Pregnancy Category C. Animal reproduction studies have not been conducted with epinephrine. It is also not known whether epinephrine can cause fetal harm when administered to a pregnant woman or can affect reproduction capacity. Epinephrine should be given to a pregnant woman only if clearly needed.

Labor and Delivery. Parenteral administration of epinephrine if used to support blood pressure during low or other spinal anesthesia for delivery can cause acceleration of fetal heart rate and should not be used in obstetrics when maternal blood pressure exceeds 130/80. (See CONTRAINDICATIONS.)

ADVERSE REACTIONS

Transient and minor side effects of anxiety, headache, fear and palpitations occur only with systemic therapeutic doses, especially in hyperthyroid individuals. Adverse effects such as cardiac arrhythmias and excessive rise in blood pressure may occur with systemic therapeutic doses or with inadvertent overdosage. Other adverse reactions include cerebral hemorrhage, hemiplegia, subarachnoid hemorrhage, anginal pain in patients with angina pectoris, anxiety, restlessness, headache, tremor, weakness, dizziness, pallor and respiratory difficulty. Such reactions are unlikely when epinephrine is diluted to 1:200,000 for injection with local anesthetic agents.

OVERDOSAGE

Erroneous administration of large doses of epinephrine may lead to precordial distress, vomiting, headache, dyspnea, as well as unusually elevated blood pressure. (See WARNINGS.) Toxic effects of overdosage can be counteracted by injection of an alpha-adrenergic blocker and a beta-adrenergic blocker. In the event of a sharp rise in blood pressure, rapid-acting vasodilators such as the nitrites, or alpha-adrenergic blocking agents can be given to counteract the marked pressor effect of large doses of epinephrine.

DOSAGE AND ADMINISTRATION

Subcutaneously or intramuscularly – 0.2 to 1 mL (mg). Start with a small dose and increase if required.

Note: The subcutaneous is the preferred route of administration. If given intramuscularly, injection into the buttocks should be avoided.

Hypersensitivity Reactions

For bronchial asthma and certain allergic manifestations, e.g., angioedema, urticaria, serum sickness, anaphylactic shock, use epinephrine subcutaneously. The adult intravenous dose for hypersensitivity reactions or to relieve bronchospasm usually ranges from 0.1 to 0.25 mg injected slowly. Neonates may be given a dose of 0.01 mg per kg of body weight; for the infant 0.05 mg is an adequate initial dose and this may be repeated at 20 to 30 minute intervals in the management of asthma attacks.

Cardiac Resuscitation

A dose of 0.5 mL (0.5 mg) diluted to 10 mL with sodium chloride injection can be administered intravenously or intracardially to restore myocardial contractility.

Intracardiac injection should only be administered by personnel well trained in the technique, if there has not been sufficient time to establish an intravenous route.

External cardiac massage should follow intracardial administration to permit the drug to enter coronary circulation. The drug should be used secondarily to unsuccessful attempts with physical or electromechanical methods.

Ophthalmologic Use

Ophthalmologic use (for producing conjunctival decongestion, to control hemorrhage, produce mydriasis and reduce intraocular pressure) – use a concentration of 1:10,000 (0.1 mg/mL) to 1:1000 (1 mg/mL).

Regional Anesthesia

A final concentration of 1:200,000 of epinephrine injection is recommended for infiltration injection, nerve block, caudal or other epidural blocks. From 0.3 to 0.4 mg of epinephrine (0.3 to 0.4 mL of 1:1000 solution) may be mixed with spinal anesthetic agents.

Parenteral drug products should be inspected visually for particulate matter and discoloration prior to administration. (See PRECAUTIONS.)

HOW SUPPLIED

Epinephrine Injection, USP 1:1000 (1 mg/mL) is supplied in a 1 mL ampul single-dose container (NDC 0409-7241-61).

Store at 20 to 25°C (68 to 77°F). [See USP Controlled Room Temperature.]

Protect from light.

Revised: October, 2008

Printed in USA EN-1927

Hospira, Inc., Lake Forest, IL 60045 USA

Repackaged in 2 ampule packages NDC: 70385-2008-2

Package Label & Ampule Label

Package Label

Ampule Label